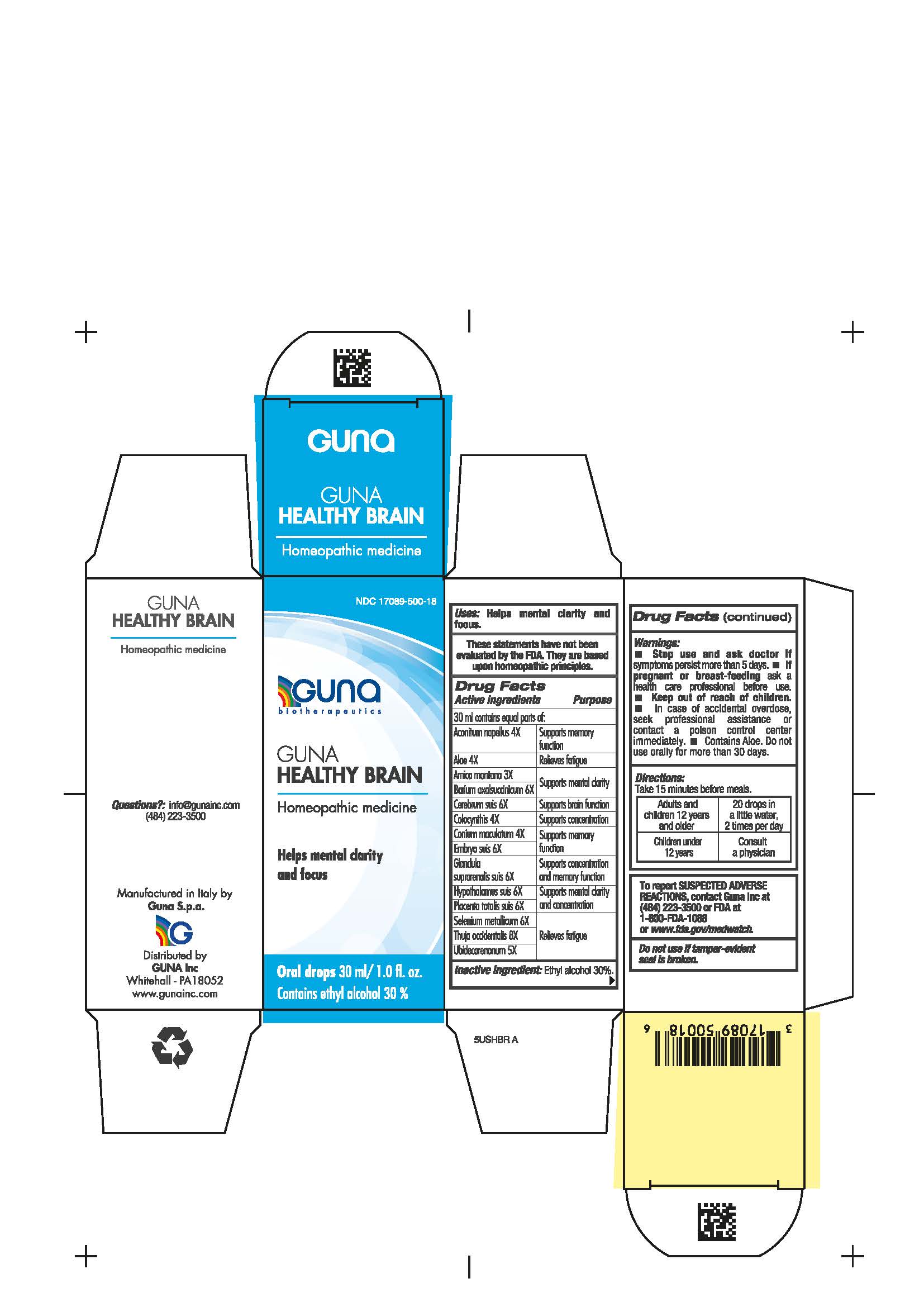 DRUG LABEL: GUNA HEALTHY BRAIN
NDC: 17089-500 | Form: SOLUTION/ DROPS
Manufacturer: Guna spa
Category: homeopathic | Type: HUMAN OTC DRUG LABEL
Date: 20210217

ACTIVE INGREDIENTS: CITRULLUS COLOCYNTHIS FRUIT PULP 4 [hp_X]/30 mL; SUS SCROFA EMBRYO 6 [hp_X]/30 mL; SUS SCROFA ADRENAL GLAND 6 [hp_X]/30 mL; SUS SCROFA PLACENTA 6 [hp_X]/30 mL; SELENIUM 6 [hp_X]/30 mL; THUJA OCCIDENTALIS LEAFY TWIG 8 [hp_X]/30 mL; CONIUM MACULATUM FLOWERING TOP 4 [hp_X]/30 mL; ACONITUM NAPELLUS 4 [hp_X]/30 mL; ALOE 4 [hp_X]/30 mL; BARIUM OXALOSUCCINATE 6 [hp_X]/30 mL; SUS SCROFA CEREBRUM 6 [hp_X]/30 mL; ARNICA MONTANA 3 [hp_X]/30 mL; SUS SCROFA HYPOTHALAMUS 6 [hp_X]/30 mL; UBIDECARENONE 5 [hp_X]/30 mL
INACTIVE INGREDIENTS: ALCOHOL 9 mL/30 mL

GUNA HEALTHY BRAIN

WARNINGS

- Stop use and ask doctor if symptoms worsen or persist more than 5 days.
- If pregnant or breast-feeding ask a health care professional before use.
- Keep out of reach of children.
- In case of accidental overdose, seek professional assistance or contact a poison control center immediately.
- Contains Aloe. Do not use orally for more than 30 days.
- Contains ethyl alcohol 30%

PREGNANCY

If pregnant or breast-feeding ask a health care profesisonal before use.

DIRECTIONS

Take 15 minutes before meals.

Adults and children twelve years and older: 20 drops in a little water, 2 times per day

Children under 12 years: consult a physician

INDICATIONS AND USAGE

Take 15 minutes before meals.

WARNINGS

Keep out of reach of children.

QUESTIONS

info@gunainc.com
(484) 223-3500

Inactive ingredient: Ethyl alcohol 30%.

ACTIVE INGREDIENTS/PURPOSE

Aconitum napellus 4X Supports memory function

Aloe 4X Relieves fatigue

Arnica montana 3X Supports mental clarity

Barium oxalsuccinicum 6X Supports mental clarity

Cerebrum suis 6X Supports brain function

Colocynthis 4X Supports concentration

Conium maculatum 4X Supports memory function

Embryo suis 6X Supports memory function

Glandula suprarenalis suis 6X Supports concentration and memory function

Hypothalamus suis 6X Supports mental clarity and concentration

Placenta totalis suis 6X Supports mental clarity and concentration

Selenium metallicum 6X Relieves fatigue

Thuja occidentalis 8X Relieves fatigue

Ubidecarenonum 5X Relieves fatigue

USES

- Helps mental clarity and focus